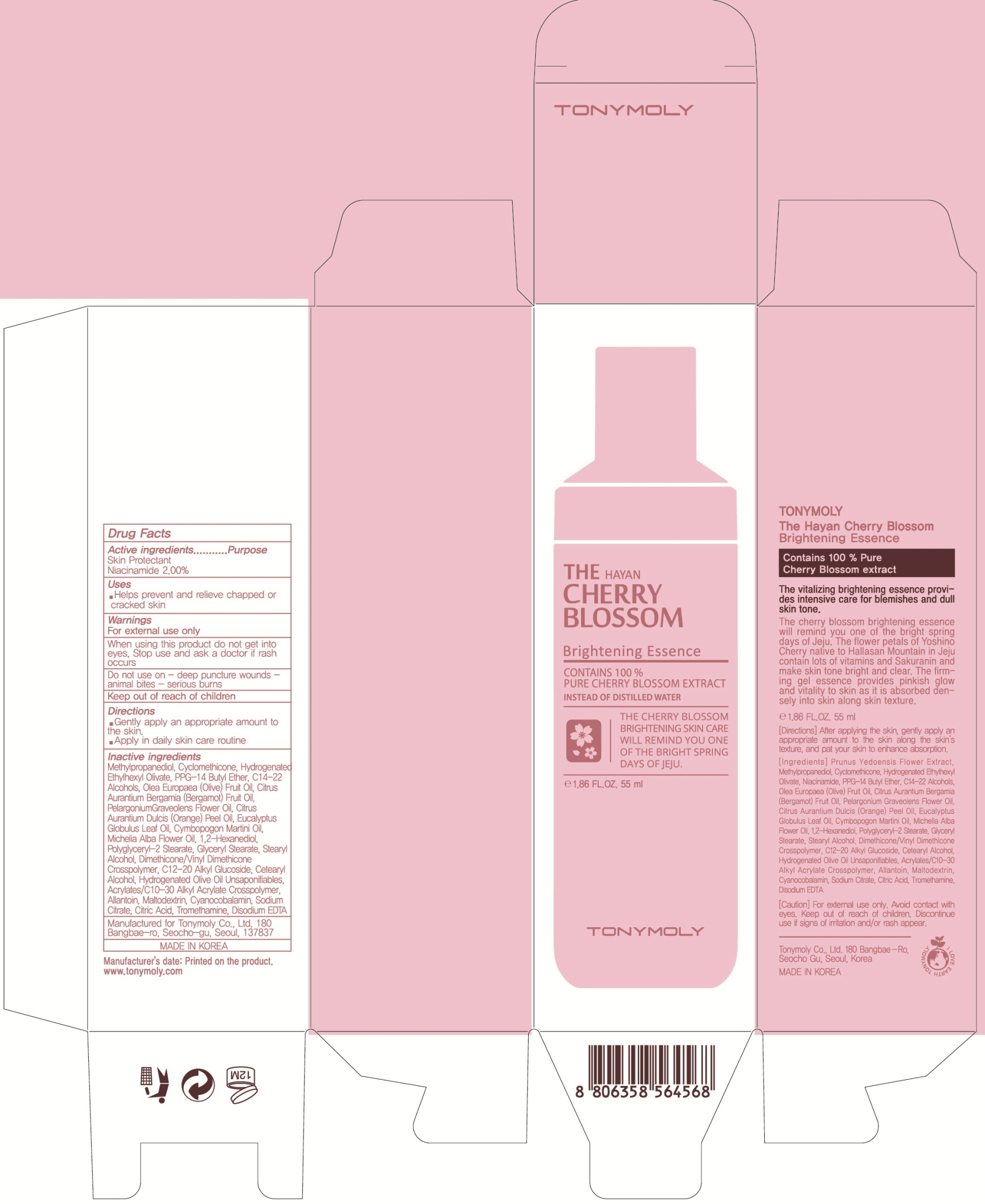 DRUG LABEL: The Hayan Cherry Blossom Brightening Essence
NDC: 59078-303 | Form: CREAM
Manufacturer: TONYMOLY CO.,LTD
Category: otc | Type: HUMAN OTC DRUG LABEL
Date: 20160601

ACTIVE INGREDIENTS: Niacinamide 1.1 g/55 mL
INACTIVE INGREDIENTS: Methylpropanediol; Cyclomethicone

ACTIVE INGREDIENT

Active ingredient: Niacinamide 2.00%

INACTIVE INGREDIENT

Inactive Ingredient: Prunus Yedoensis Flower Extract, Methylpropanediol, Cyclomethicone, Hydrogenated Ethylhexyl Olivate, PPG-14 Butyl Ether, C14-22 Alcohols, Olea Europaea (Olive) Fruit Oil, Citrus Aurantium Bergamia (Bergamot) Fruit Oil, Pelargonium Graveolens Flower Oil, Citrus Aurantium Dulcis (Orange) Peel Oil, Eucalyptus Globulus Leaf Oil, Cymbopogon Martini Oil, Michelia Alba Flower Oil, 1,2-Hexanediol, Polyglyceryl-2 Stearate, Glyceryl Stearate, Stearyl Alcohol, Dimethicone/Vinyl Dimethicone Crosspolymer, C12-20 Alkyl Glucoside, Cetearyl Alcohol, Hydrogenated Olive Oil Unsaponifiables, Acrylates/C10-30 Alkyl Acrylate Crosspolymer, Allantoin, Maltodextrin, Cyanocobalamin, Sodium Citrate, Citric Acid, Tromethamine, Disodium EDTA

PURPOSE

Purpose: Skin Protectant

WARNINGS

Warnings: For external use only. When using this product do not get into eyes. Stop use and ask a doctor if rash occurs. Do not use on - deep puncture wounds - animal bites - serious burns Keep out of reach of children.

KEEP OUT OF REACH OF CHILDREN

Use

Use: helps prevent and relieve chapped or cracked skin

Directions

Directions: - Gently apply an appropriate amount to the skin. - Apply in daily skin care routine